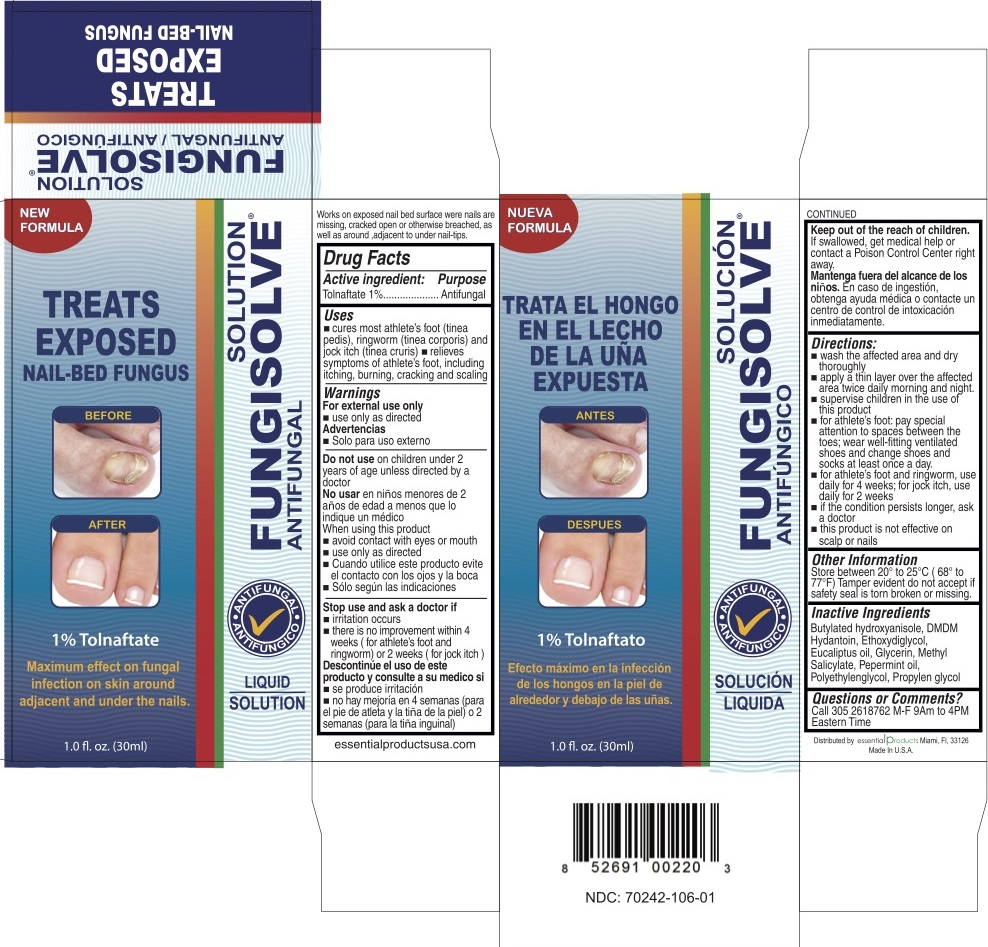 DRUG LABEL: FUNGISOLVE TOLNAFTATE ANTIFUNGAL
NDC: 70242-106 | Form: LIQUID
Manufacturer: Dannso Corp./d.b.a. Essential Products
Category: otc | Type: HUMAN OTC DRUG LABEL
Date: 20160430

ACTIVE INGREDIENTS: TOLNAFTATE 10 mg/1 mL
INACTIVE INGREDIENTS: BUTYLATED HYDROXYANISOLE
					; DMDM HYDANTOIN
					; DIETHYLENE GLYCOL MONOETHYL ETHER
					; EUCALYPTUS OIL
					; GLYCERIN; METHYL SALICYLATE
					; PEPPERMINT OIL
					; POLYETHYLENE GLYCOLS
					; PROPYLENE GLYCOL
					

FUNGISOLVE Tolnaftate Antifungal

Active Ingredients

Tolnaftate 1%

Purpose

Antifungal

Uses

cures most athlete's foot (tinea pedis), ringworm (tinea corporis) and jock itch (tinea cruris)

relieves sympotoms of athelete's foot including itching, burning, cracking and scaling.

Warnings

For external use only use only as directed

Do not use

- children under 2 years of age unless directed by a doctor

When using this product

- avoid contact with the eyes or mouth
- use only as directed

Stop use and ask a doctor if

- irritation occurs
- there is no improvement within 4 weeks (for athelete's foot and ringworm) or 2 weeks (for jock itch)

Keep out of reach of children.

If swallowed, get medical help or contact a Poison Control Center right away.

Directions

- wash the affected area and dry thoroughtly
- apply a thin layer over the affected area twice daily morning and night
- supervice children in the use of this product
- for athlete's foot, pay special attention to spaces between the toes: wear well-fitting ventilated shoes and change shoes and socks at least once a day.
- for athlete's foot and ringworm, use daily for 4 weeks; for jock itch, use daily for 2 weeks
- if the condiotion persists longer, ask a doctor
- this product is not effective on scalp or nails

Other Information

store between 20 to 25 C (68 to 77)F

Tamper evident do not accept if safety seal is broken or missing.

Inactive Ingredients

Butylated hydroxyanisole, DMDM Hyantoin, Ethoxydiglycol, Eucaliptu oil, Glycerin, Methyl Sallicylate, Pepermint oil, Polyethylene Glycol, Propylen glycol.

Questions or Comments?

Call 305 2618762 M-F 9AM to 4PM Eastern Time

Distributed by:

Essential Productd Miami, FL, 33126 www.essentialproductsusa.com